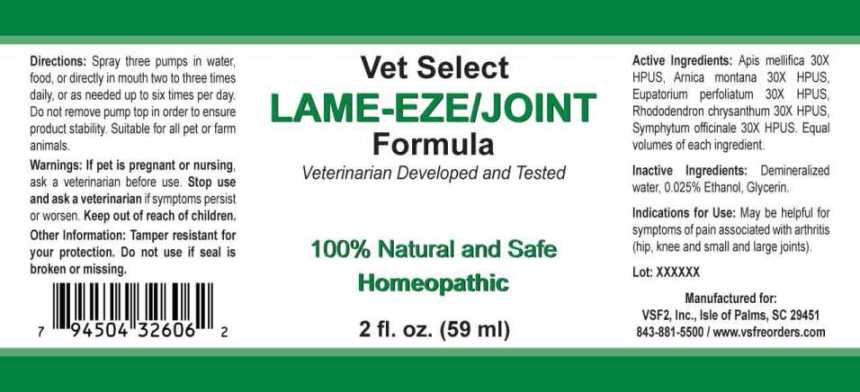 DRUG LABEL: Lame-Eze/Joint
NDC: 86100-0003 | Form: LIQUID
Manufacturer: Vsf2, Inc.
Category: homeopathic | Type: OTC ANIMAL DRUG LABEL
Date: 20251110

ACTIVE INGREDIENTS: APIS MELLIFERA 30 [hp_X]/1 mL; ARNICA MONTANA 30 [hp_X]/1 mL; EUPATORIUM PERFOLIATUM FLOWERING TOP 30 [hp_X]/1 mL; RHODODENDRON AUREUM LEAF 30 [hp_X]/1 mL; COMFREY ROOT 30 [hp_X]/1 mL
INACTIVE INGREDIENTS: WATER; ALCOHOL

Drug Facts:

ACTIVE INGREDIENTS:

Apis Mellifica 30X HPUS, Arnica Montana 30X HPUS, Eupatorium Perfoliatum 30X HPUS, Rhododendron Chrysanthum 30X HPUS, Symphytum Officinale 30X HPUS.

Equal volumes of each ingredient.

INDICATIONS FOR USE:

May be helpful for symptoms of pain associated with arthritis (hip, knee and small and large joints).

WARNINGS:

If pet is pregnant or nursing, ask a veterinarian before use.

Stop use and ask a veterinarian if symptoms persist or worsen.

Keep out of reach of children.

Other Information: Tamper resistant for your protection. Do not use if seal is broken or missing.

KEEP OUT OF THE REACH OF CHILDREN:

Keep out of reach of children.

DIRECTIONS:

Spray three pumps in water, food or directly in mouth two to three times daily, or as needed up to six times per day. Do not remove pump top in order to ensure product stability. Suitable for all pet or farm animals.

INDICATIONS FOR USE:

May be helpful for symptoms of pain associated with arthritis (hip, knee and small and large joints).

INACTIVE INGREDIENTS:

Demineralized water, 0.025% Ethanol, Glycerin.

QUESTIONS:

Manufactured for:

VSF2, Inc., Isle of Palms, SC 29451

843-881-5500 / www.vsfreorders.com

PACKAGE LABEL DISPLAY:

Vet Select

LAME-EZE/JOINT

Formula

Veterinarian Developed and Tested

100% Natural and Safe

Homeopathic

2 fl. oz. (59 ml)